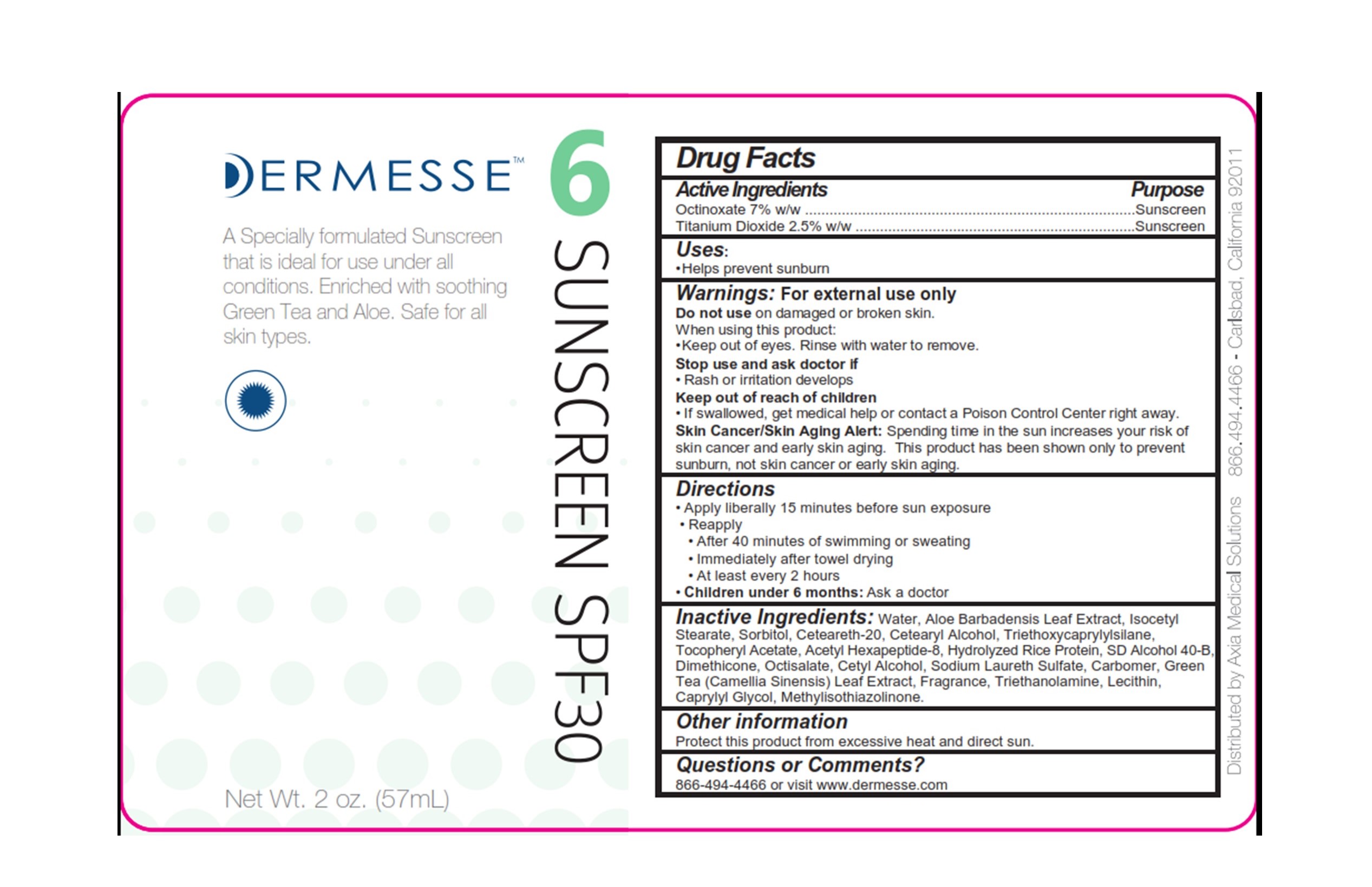 DRUG LABEL: Dermesse Sunscreen SPF30
NDC: 68723-330 | Form: LOTION
Manufacturer: Axia Medical Solutions, LLC
Category: otc | Type: HUMAN OTC DRUG LABEL
Date: 20210712

ACTIVE INGREDIENTS: OCTINOXATE 70 mg/1 g; TITANIUM DIOXIDE 20 mg/1 g
INACTIVE INGREDIENTS: WATER; ISOCETYL STEARATE; SORBITOL; CETOSTEARYL ALCOHOL; POLYOXYL 20 CETOSTEARYL ETHER; .ALPHA.-TOCOPHEROL ACETATE; ACETYL HEXAPEPTIDE-8; ALCOHOL; DIMETHICONE 350; OCTISALATE; CETYL ALCOHOL; METHICONE (20 CST); SODIUM LAURETH SULFATE; CARBOMER INTERPOLYMER TYPE A (ALLYL SUCROSE CROSSLINKED); GREEN TEA LEAF; TROLAMINE; STEARIC ACID; LECITHIN, SOYBEAN; ALUMINUM OXIDE; CAPRYLYL GLYCOL; METHYLISOTHIAZOLINONE

Dermessse Sunscreen SPF30

Active Ingredients

Octinoxiate 7% w/w

Titanium Dioxide 2% w/w

Purpose

Sunscreen

Uses:

• Helps prevent sunburn

Warnings:

For external use only

Do not use on damaged or broken skin.

When using this product:

• Keep out of eyes. Rinse with water to remove.

Stop use and ask doctor if

• Rash or irritation develops

Keep out of reach of children

• If swallowed, get medical help or contact a Poison Control Center right away.

WARNINGS

Skin Cancer/Skin Aging Alert: Spending time in the sun increases your risk of skin cancer and early skin aging. This product has been shown only to prevent sunburn, not skin cancer or early skin aging.

Directions

• Apply liberally 15 minutes before sun exposure

• Reapply

• After 40 minutes of swimming or sweating

• Immediately after towel drying

• At least every 2 hours

Children under 6 months: Ask a doctor

Inactive Ingredients

Water, Aloe Barbadensis Leaf Extract, Isocetyl Stearate, Sorbitol, Cetearyl Alcohol, Ceteareth-20, Tocopheryl Acetate, Acetyl Hexapdptide-8, Hydrolyzed Rice Protein, Alcohol SDA-40, Dimethicone, Octyl Salicylate, Cety Alcohol, Methicone, Sodium Laureth Sulfate, Carbomer, Green Tea (Carnellia Sinensis) Leaf Extract, Fragrance, Triethanolamine, Stearic Acid, Lecithin, Alumina, Caprylyl Glycol, Methylisothiazolinone

Other information

Protect this product from excessive heat and direct sun.

Questions or Comments?

866-494-4466 or visit www.dermesse.com